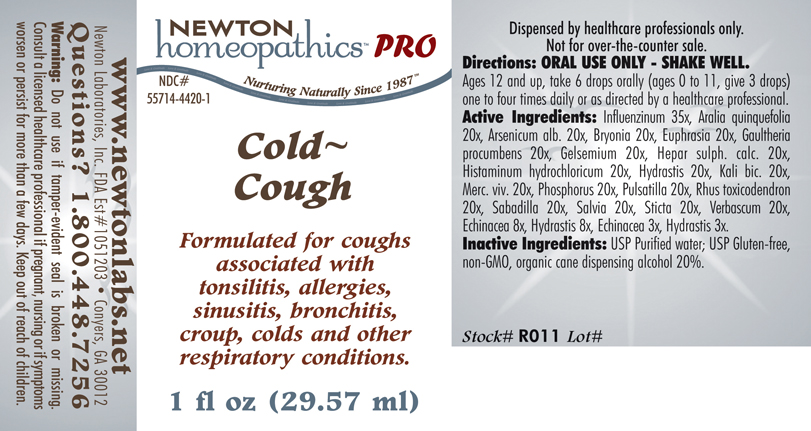 DRUG LABEL: Cold  Cough 
NDC: 55714-4420 | Form: LIQUID
Manufacturer: Newton Laboratories, Inc.
Category: homeopathic | Type: HUMAN PRESCRIPTION DRUG LABEL
Date: 20110601

ACTIVE INGREDIENTS: Influenza A Virus 35 [hp_X]/1 mL; American Ginseng 20 [hp_X]/1 mL; Arsenic Trioxide 20 [hp_X]/1 mL; Bryonia Alba Root 20 [hp_X]/1 mL; Euphrasia Stricta 20 [hp_X]/1 mL; Gaultheria Procumbens Top 20 [hp_X]/1 mL; Gelsemium Sempervirens Root 20 [hp_X]/1 mL; Calcium Sulfide 20 [hp_X]/1 mL; Histamine Dihydrochloride 20 [hp_X]/1 mL; Goldenseal 20 [hp_X]/1 mL; Potassium Dichromate 20 [hp_X]/1 mL; Mercury 20 [hp_X]/1 mL; Phosphorus 20 [hp_X]/1 mL; Pulsatilla Vulgaris 20 [hp_X]/1 mL; Toxicodendron Pubescens Leaf 20 [hp_X]/1 mL; Schoenocaulon Officinale Seed 20 [hp_X]/1 mL; Sage 20 [hp_X]/1 mL; Lobaria Pulmonaria 20 [hp_X]/1 mL; Verbascum Thapsus 20 [hp_X]/1 mL; Echinacea, Unspecified 8 [hp_X]/1 mL; Goldenseal 8 [hp_X]/1 mL; Influenza B Virus 35 [hp_X]/1 mL
INACTIVE INGREDIENTS: Alcohol

Cold Cough

PRODUCT NAME & INDICATIONS SECTION

Cold Cough Formulated for coughs associated with tonsilitis, allergies, sinusitis, bronchitis, croup, colds and other respiratory conditions.

DIRECTION SECTION

Directions: ORAL USE ONLY - SHAKE WELL. Ages 12 and up, take 6 drops orally (ages 0 to 11, give 3 drops) one to four times daily or as directed by a healthcare professional.

ACTIVE INGREDIENT SECTION

Influenzinum 35x, Aralia quinquefolia 20x, Arsenicum alb. 20x, Bryonia 20x, Euphrasia 20x, Gaultheria procumbens 20x, Gelsemium 20x, Hepar sulph. calc. 20x, Histaminum hydrochloricum 20x, Hydrastis 20x, Kali bic. 20x, Merc. viv. 20x, Phosphorus 20x, Pulsatilla 20x, Rhus toxicodendron 20x, Sabadilla 20x, Salvia 20x, Sticta 20x, Verbascum 20x, Echinacea 8x, Hydrastis 8x, Echinacea 3x, Hydrastis 3x.

PURPOSE SECTION

Formulated for coughs associated with tonsilitis, allergies, sinusitis, bronchitis, croup, colds and other respiratory conditions.

INACTIVE INGREDIENT SECTION

Inactive Ingredients: USP Purified Water; USP Gluten-free, non-GMO, organic cane dispensing alcohol 20%.

QUESTIONS? SECTION

www.newtonlabs.net Newton Laboratories, Inc. FDA Est # 1051203 - Conyers, GA 30012
Questions? 1.800.448.7256

WARNINGS SECTION

Warning: Do not use if tamper- evident seal is broken or missing. Consult a licensed healthcare professional if pregnant, nursing or if symptoms worsen or persist for more than a few days. Keep out of reach of children.

OTC - PREGNANCY OR BREAST FEEDING SECTION

Consult a licensed healthcare professional if pregnant, nursing or if symptoms worsen or persist for more than a few days.

OTC - KEEP OUT OF REACH OF CHILDREN SECTION

Keep out of reach of children